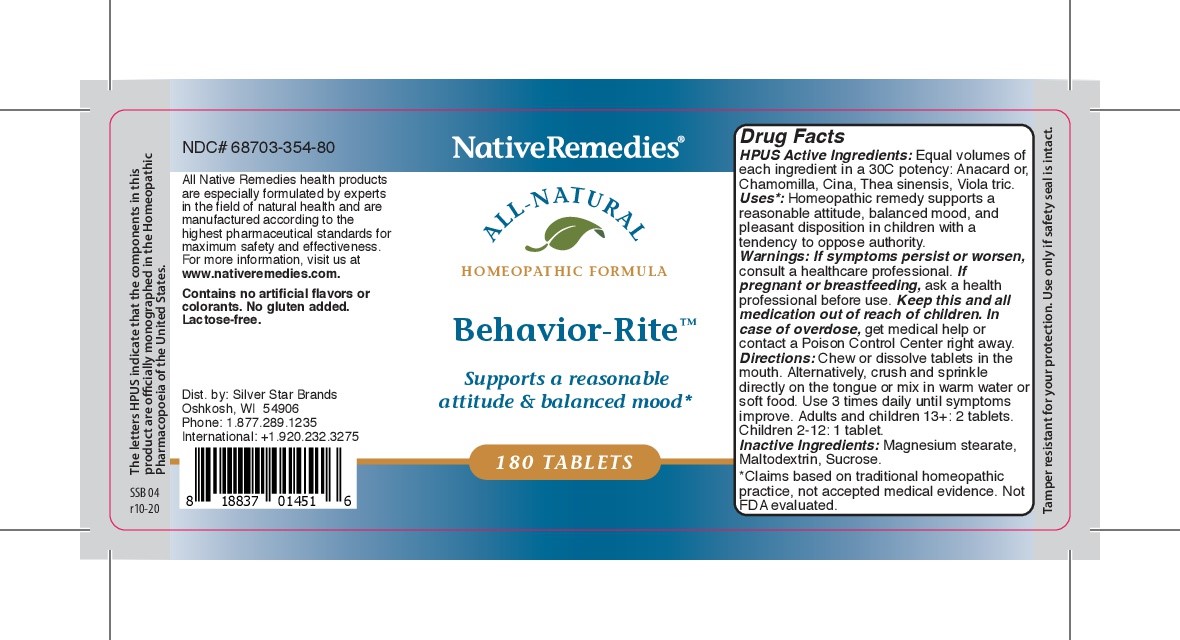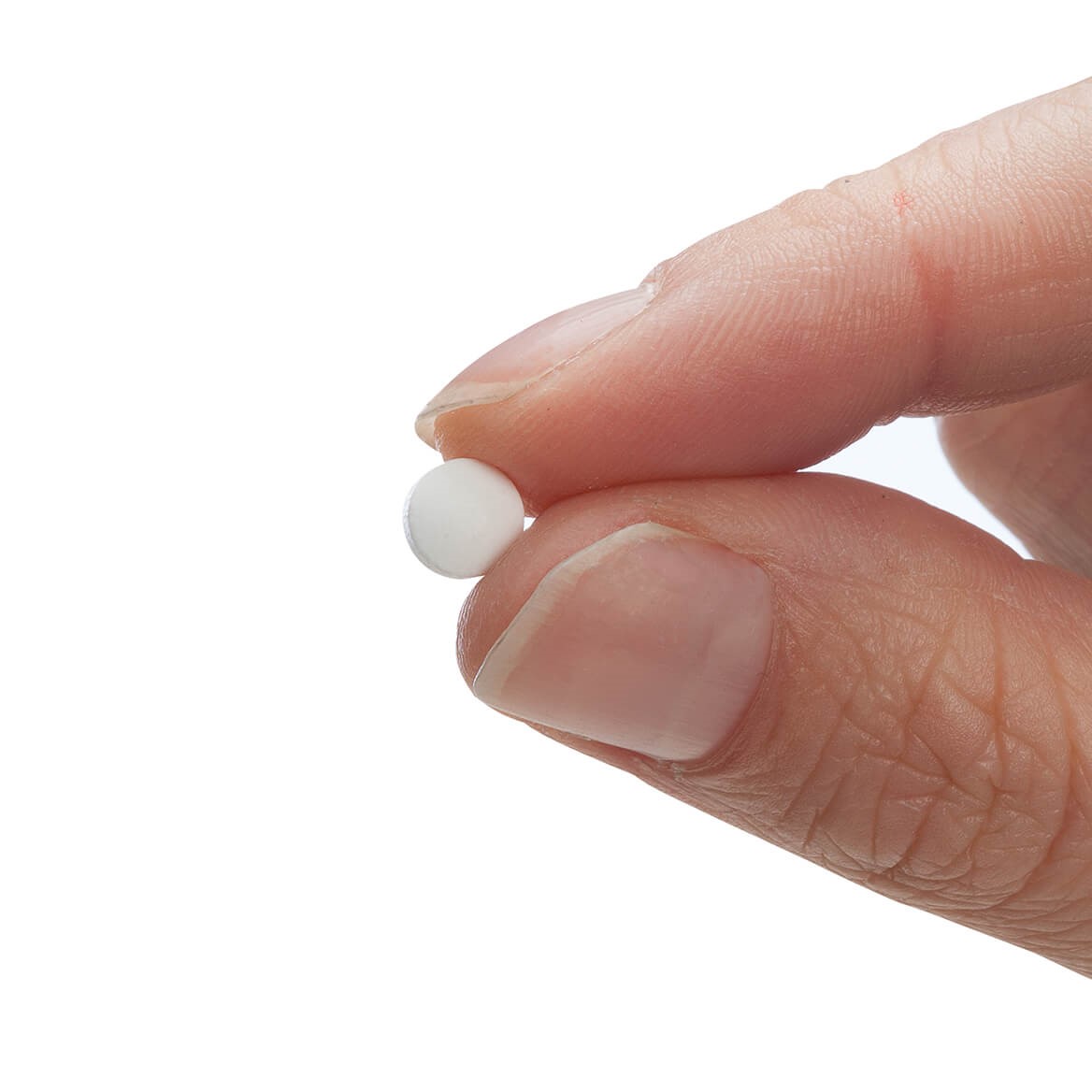 DRUG LABEL: Behavior-Rite
NDC: 68703-354 | Form: TABLET
Manufacturer: Silver Star Brands
Category: homeopathic | Type: HUMAN OTC DRUG LABEL
Date: 20250101

ACTIVE INGREDIENTS: ARTEMISIA MARITIMA FLOWER 30 [hp_C]/180 1; CAMELLIA SINENSIS FLOWER 30 [hp_C]/180 1; MATRICARIA RECUTITA 30 [hp_C]/180 1; VIOLA TRICOLOR 30 [hp_C]/180 1; ANACARDIUM OCCIDENTALE FRUIT 30 [hp_C]/180 1
INACTIVE INGREDIENTS: MAGNESIUM STEARATE; SUCROSE; MALTODEXTRIN

NativeRemedies® Behavior-Rite™

HPUS Active Ingredients: Anacard or, Chamomilla, Cina, Thea sinensis, Viola tric.

Uses*

Uses*: Homeopathic remedy supports a reasonable attitude, balanced mood, and pleasant disposition in children with a tendency to oppose authority.

* Claims based on traditional homeopathic practice, not accepted medical evidence. Not FDA evaluated.

Warnings

Warnings: If symptoms persist or worsen, consulta healthcare professional. If pregnant or breastfeeding, ask a health professional before use. Keep this and all medication out of reach of children. In case of overdose, get medical help or contact a Poison Control Center right away.

Directions

Directions: Chew or dissolve tablets in the mouth. Alternatively crush and sprinkle directly on the tongue or mix in warm waater or soft food. Use 3 times daily until symptoms improve. Adults and children 13+: 2 tablets. Children 2-12: 1 tablet.

OTHER SAFETY INFORMATION

Tamper resistant for yoru protection. Ue only if safety seal is intact.

Contains no artificial flavors or colorants. No gluten added. Lactose-free.

Inactive Ingredients

Inactive Ingredients: Magnesium stearate, Maltodextrin, Sucrose.

KEEP OUT OF REACH OF CHILDREN

Keep this and all medication our of reach of children.

PREGNANCY OR BREAST FEEDING

If pregnant or breastfeeding, ask a health professional before use.

PURPOSE

Supports a reasonable attitude & balanced mood.